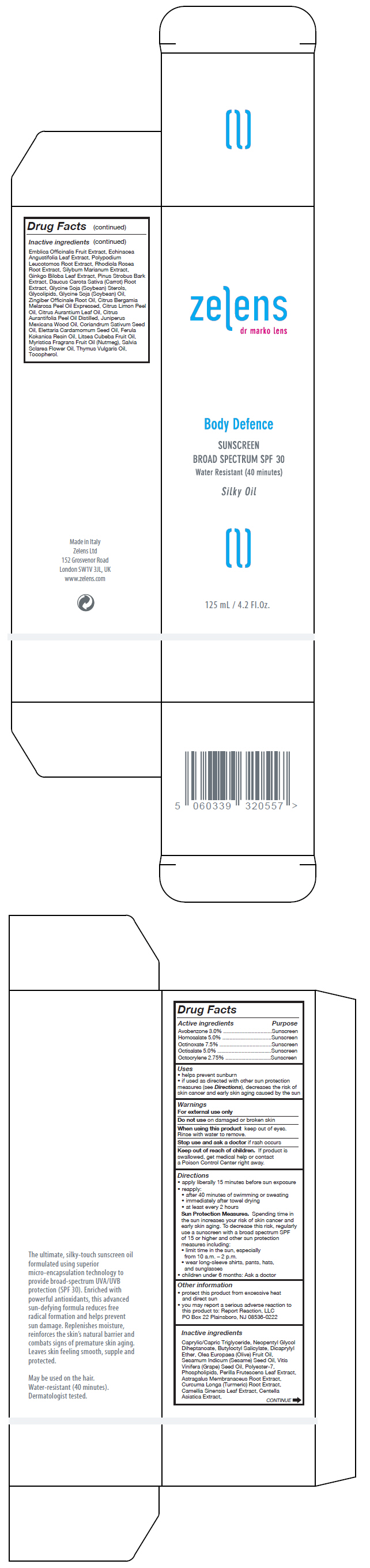 DRUG LABEL: BODY DEFENCE SUNSCREEN Broad Spectrum SPF30
NDC: 63712-201 | Form: OIL
Manufacturer: ZELENS Limited
Category: otc | Type: HUMAN OTC DRUG LABEL
Date: 20191105

ACTIVE INGREDIENTS: OCTINOXATE 75 mg/1 mL; OCTISALATE 50 mg/1 mL; HOMOSALATE 50 mg/1 mL; AVOBENZONE 30 mg/1 mL; OCTOCRYLENE 27.5 mg/1 mL
INACTIVE INGREDIENTS: MEDIUM-CHAIN TRIGLYCERIDES; NEOPENTYL GLYCOL DIHEPTANOATE; BUTYLOCTYL SALICYLATE; DICAPRYLYL ETHER; OLIVE OIL; SESAME OIL; GRAPE SEED OIL; POLYESTER-7; LECITHIN, SOYBEAN; PERILLA FRUTESCENS LEAF; ASTRAGALUS PROPINQUUS ROOT; TURMERIC; GREEN TEA LEAF; CENTELLA ASIATICA; ECHINACEA ANGUSTIFOLIA LEAF; GINKGO; PINUS STROBUS BARK; PHYLLANTHUS EMBLICA FRUIT; PHLEBODIUM AUREUM ROOT; SEDUM ROSEUM ROOT; MILK THISTLE; CARROT; SOY STEROL; SOYBEAN OIL; GINGER; BERGAMOT OIL; LEMON OIL; BITTER ORANGE OIL; LIME OIL; CEDRUS ATLANTICA BARK OIL; CORIANDER OIL; CARDAMOM OIL; GALBANUM OIL; LITSEA OIL; NUTMEG OIL; CLARY SAGE OIL; THYME OIL; TOCOPHEROL

BODY DEFENCE SUNSCREEN Broad Spectrum SPF30

Drug Facts

ACTIVE INGREDIENT

Active ingredients | Purpose
Avobenzone 3.0% | Sunscreen
Homosalate 5.0% | Sunscreen
Octinoxate 7.5% | Sunscreen
Octisalate 5.0% | Sunscreen
Octocrylene 2.75% | Sunscreen

Uses

- helps prevent sunburn
- if used as directed with other sun protection measures (see Directions), decreases the risk of skin cancer and early skin aging caused by the sun

Warnings

For external use only

Do not use on damaged or broken skin

When using this product keep out of eyes. Rinse with water to remove.

Stop use and ask a doctor if rash occurs

Keep out of reach of children. If product is swallowed, get medical help or contact a Poison Control Center right away.

Directions

- apply liberally 15 minutes before sun exposure
- reapply:
  - after 40 minutes of swimming or sweating
  - immediately after towel drying
  - at least every 2 hours
  Sun Protection Measures. Spending time in the sun increases your risk of skin cancer and early skin aging. To decrease this risk, regularly use a sunscreen with a broad spectrum SPF of 15 or higher and other sun protection measures including:
  - limit time in the sun, especially from 10 a.m. – 2 p.m.
  - wear long-sleeve shirts, pants, hats, and sunglasses
- children under 6 months: Ask a doctor

Other information

- protect this product from excessive heat and direct sun
- you may report a serious adverse reaction to this product to: Report Reaction, LLC
  PO Box 22 Plainsboro, NJ 08536-0222

Inactive ingredients

Caprylic/Capric Triglyceride, Neopentyl Glycol Diheptanoate, Butyloctyl Salicylate, Dicaprylyl Ether, Olea Europaea (Olive) Fruit Oil, Sesamum Indicum (Sesame) Seed Oil, Vitis Vinifera (Grape) Seed Oil, Polyester-7, Phospholipids, Perilla Frutescens Leaf Extract, Astragalus Membranaceus Root Extract, Curcuma Longa (Turmeric) Root Extract, Camellia Sinensis Leaf Extract, Centella Asiatica Extract, Emblica Officinalis Fruit Extract, Echinacea Angustifolia Leaf Extract, Polypodium Leucotomos Root Extract, Rhodiola Rosea Root Extract, Silybum Marianum Extract, Ginkgo Biloba Leaf Extract, Pinus Strobus Bark Extract, Daucus Carota Sativa (Carrot) Root Extract, Glycine Soja (Soybean) Sterols, Glycolipids, Glycine Soja (Soybean) Oil, Zingiber Officinale Root Oil, Citrus Bergamia Melarosa Peel Oil Expressed, Citrus Limon Peel Oil, Citrus Aurantium Leaf Oil, Citrus Aurantifolia Peel Oil Distilled, Juniperus Mexicana Wood Oil, Coriandrum Sativum Seed Oil, Elettaria Cardamomum Seed Oil, Ferula Kokanica Resin Oil, Litsea Cubeba Fruit Oil, Myristica Fragrans Fruit Oil (Nutmeg), Salvia Sclarea Flower Oil, Thymus Vulgaris Oil, Tocopherol.

PRINCIPAL DISPLAY PANEL - 125 mL Bottle Box

zelens
dr marko lens

Body Defence

SUNSCREEN
BROAD SPECTRUM SPF 30
Water Resistant (40 minutes)

Silky Oil

125 mL / 4.2 Fl. Oz.